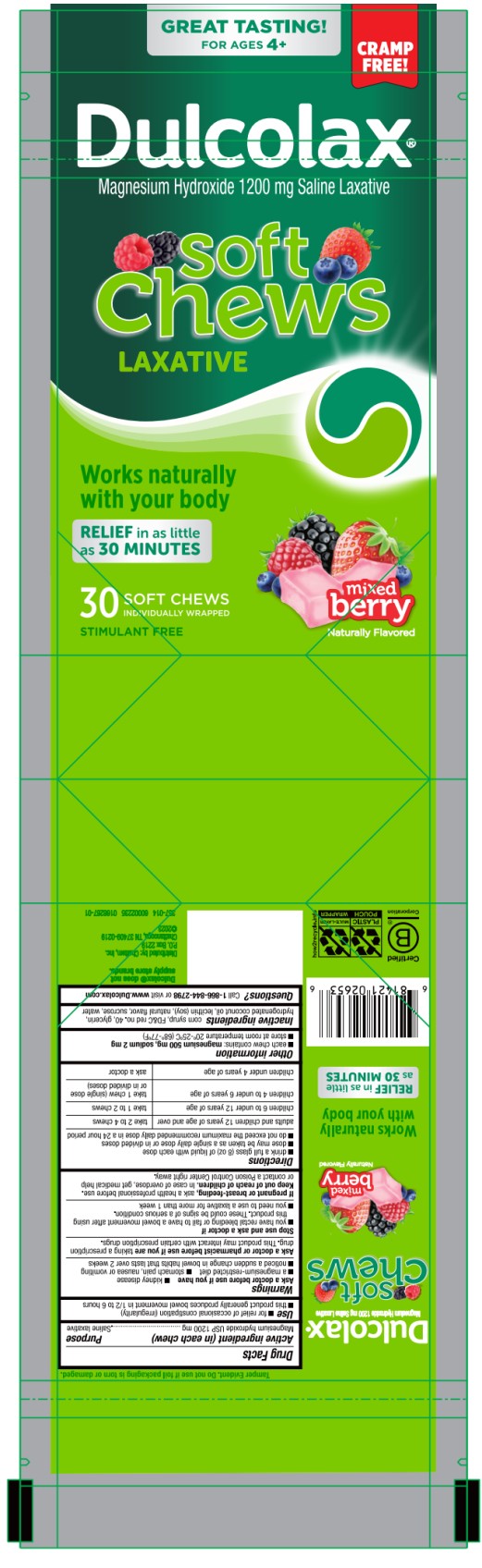 DRUG LABEL: Dulcolax Soft Chews Mixed Berry
NDC: 41167-0265 | Form: TABLET, CHEWABLE
Manufacturer: Chattem, Inc.
Category: otc | Type: HUMAN OTC DRUG LABEL
Date: 20260114

ACTIVE INGREDIENTS: MAGNESIUM HYDROXIDE 1200 mg/1 1
INACTIVE INGREDIENTS: CORN SYRUP; FD&C RED NO. 40; GLYCERIN; HYDROGENATED COCONUT OIL; LECITHIN, SOYBEAN; SUCROSE; WATER

Dulcolax Soft Chews Mixed Berry

Dulcolax® Soft Chews Saline Laxative – Mixed Berry

Drug Facts

Active ingredient (in each chew)

Magnesium hydroxide 1200 mg

Purpose

Saline laxative

Use

● for relief of occasional constipation (irregularity)

● this product generally produces bowel movement in ½ to 6 hours

Warnings

Ask a doctor before use if you have

● kidney disease ● a magnesium-restricted diet

● stomach pain, nausea or vomiting ● noticed a sudden change in bowel habits that lasts over 2 weeks

Ask a doctor or pharmacist before use if you are

taking a prescription drug. This product may interact with certain prescription drugs.

Stop use and ask a doctor if

● you have rectal bleeding or fail to have a bowel movement after using this product. These could be signs of a serious condition. ● you need to use a laxative for more than 1 week

If pregnant or breast-feeding,

ask a health professional before use.

Keep out of reach of children.

In case of overdose, get medical help or contact a Poison Control Center right away.

Directions

● drink a full glass (8 oz) of liquid with each dose

● dose may be taken as a single daily dose or in divided doses

● do not exceed the maximum recommended daily dose in a 24 hour period

adults and children 12 years of age and over | take 2 to 4 chews
children 6 to under 12 years of age | take 1 to 2 chews
children 4 to under 6 years of age | take 1 chew (single dose or in divided doses)
children under 4 years of age | ask a doctor

Other information

● each chew contains: magnesium 500 mg, sodium 2 mg

● store at room temperature 20°-25°C (68°-77°F)

Inactive ingredients

corn syrup, FD&C red no. 40, glycerin, hydrogenated coconut oil, lecithin (soy), natural flavor, sucrose, water

Questions?

Call 1-866-844-2798 or visit www.Dulcolax.com

PRINCIPAL DISPLAY PANEL

Dulcolax
Magnesium Hydroxide 1200 mg Saline Laxative
Soft
Chews
LAXATIVE
Mixed Berry
30 SOFT CHEWS